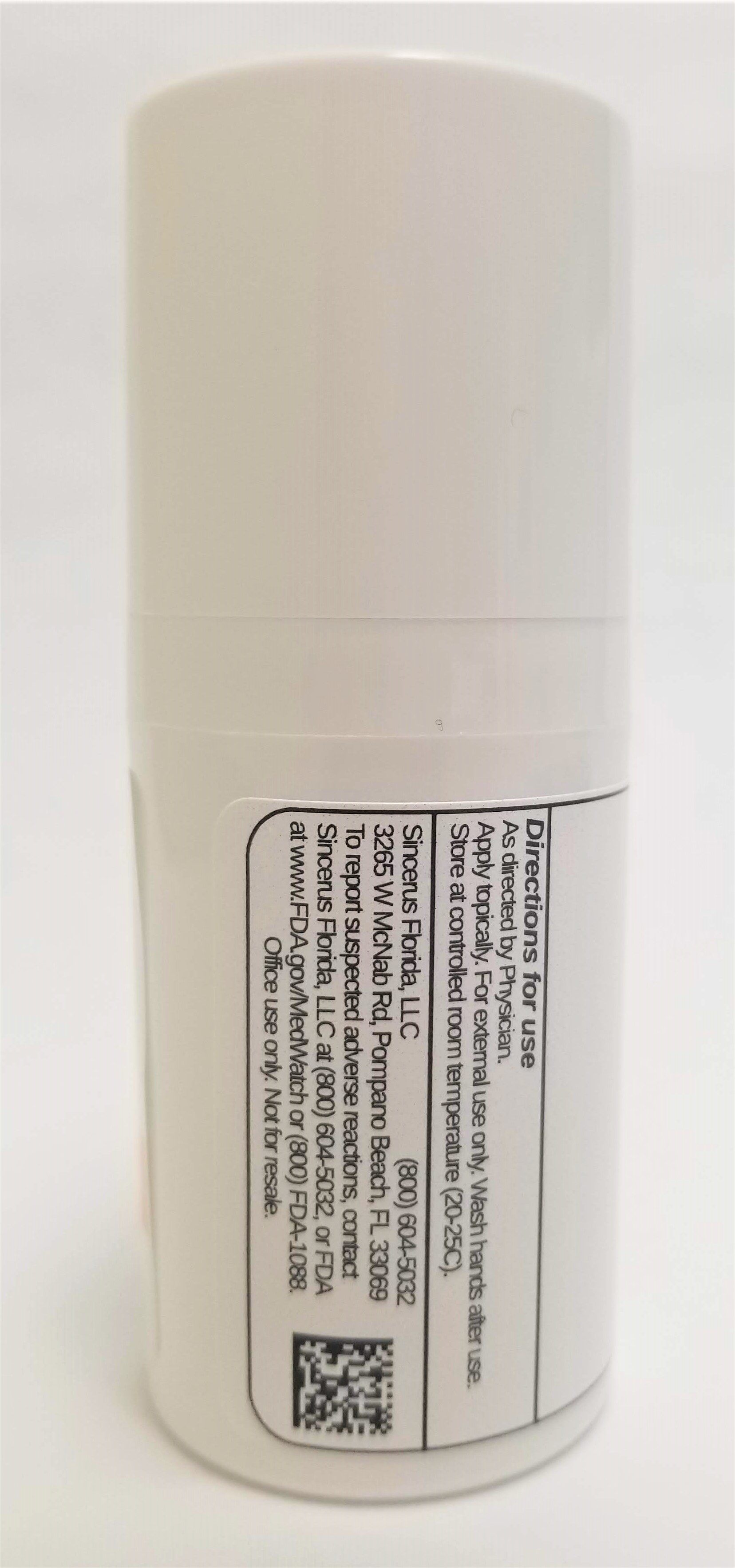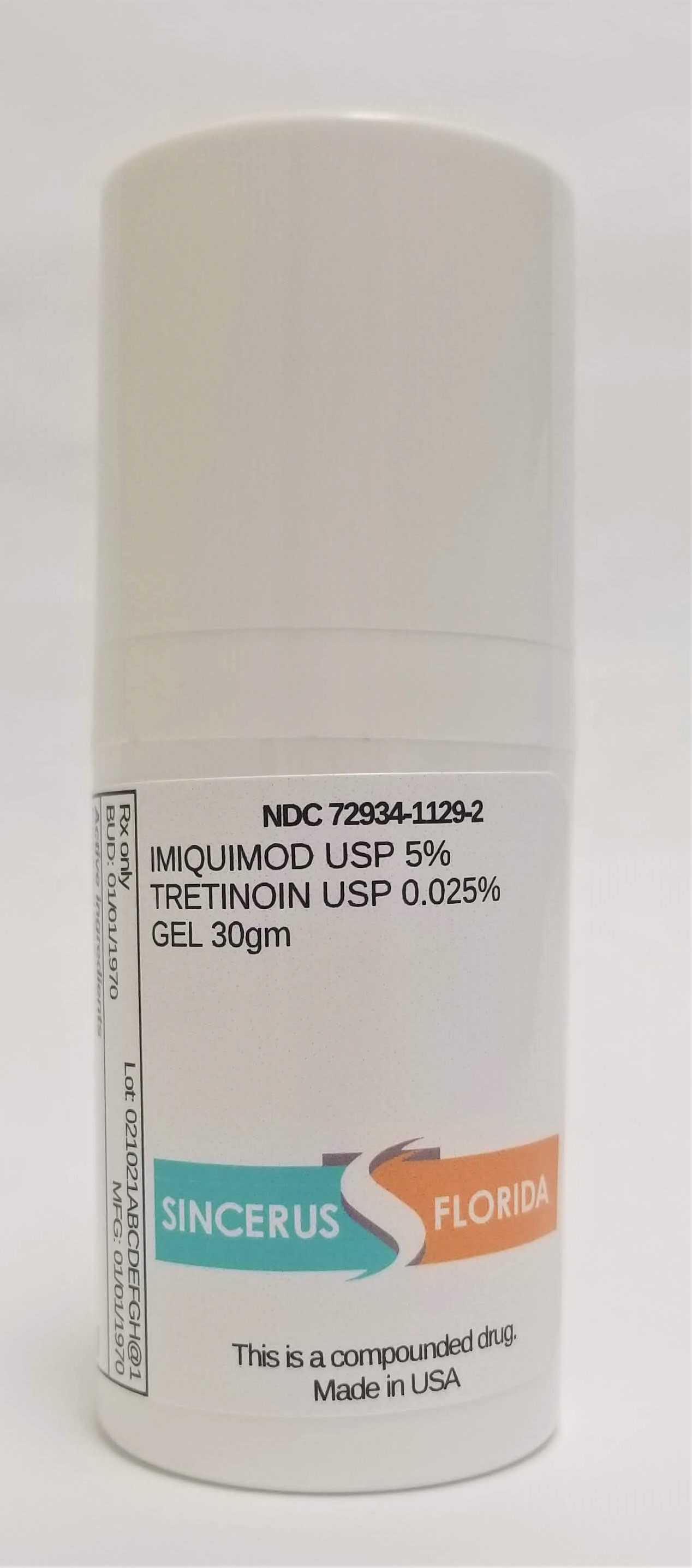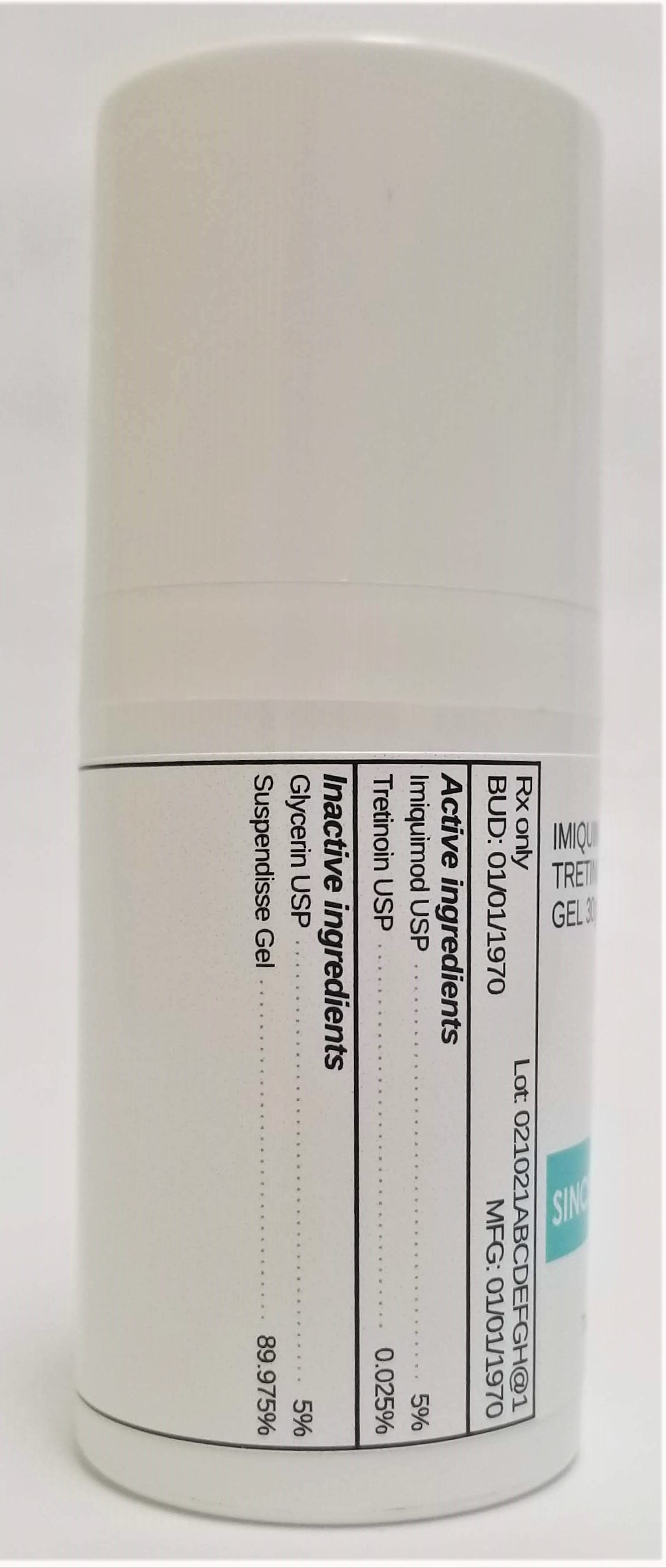 DRUG LABEL: IMIQUIMOD 5% / TRETINOIN 0.025%
NDC: 72934-1129 | Form: GEL
Manufacturer: Sincerus Florida, LLC
Category: prescription | Type: HUMAN PRESCRIPTION DRUG LABEL
Date: 20190506

ACTIVE INGREDIENTS: TRETINOIN 0.025 g/100 g; IMIQUIMOD 5 g/100 g

IMIQUIMOD 5% / TRETINOIN 0.025%